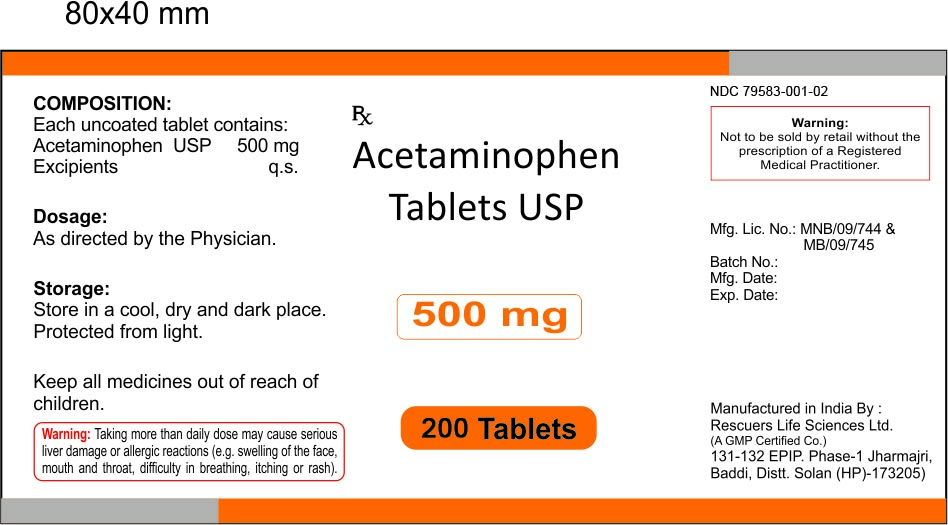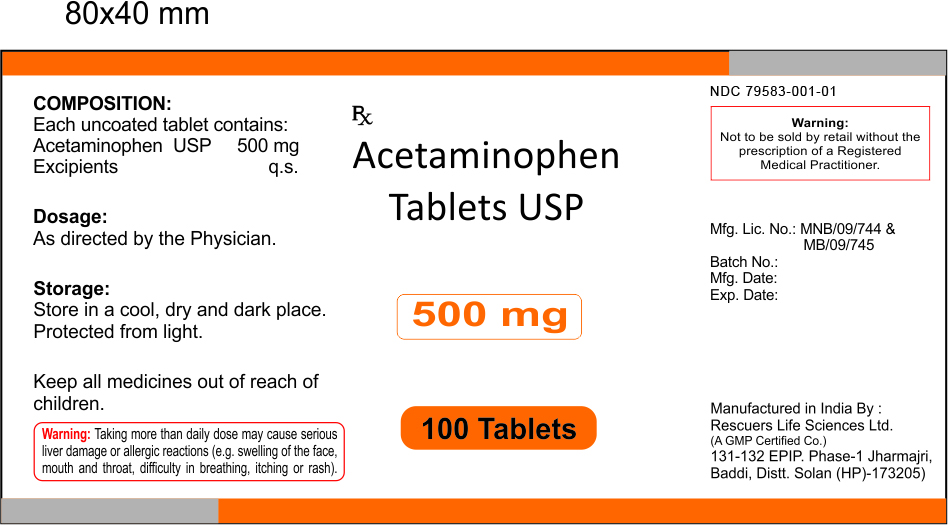 DRUG LABEL: Acetaminophen
NDC: 79583-001 | Form: TABLET
Manufacturer: Rescuers Life sciences Limited
Category: otc | Type: HUMAN OTC DRUG LABEL
Date: 20200720

ACTIVE INGREDIENTS: ACETAMINOPHEN 500 mg/1 1
INACTIVE INGREDIENTS: MICROCRYSTALLINE CELLULOSE; SODIUM LAURYL SULFATE; MAGNESIUM STEARATE; METHYLPARABEN SODIUM; STARCH, CORN; SODIUM STARCH GLYCOLATE TYPE A; CROSCARMELLOSE SODIUM; TALC; POVIDONE K30

Acetaminophen Tablets USP 500 mg